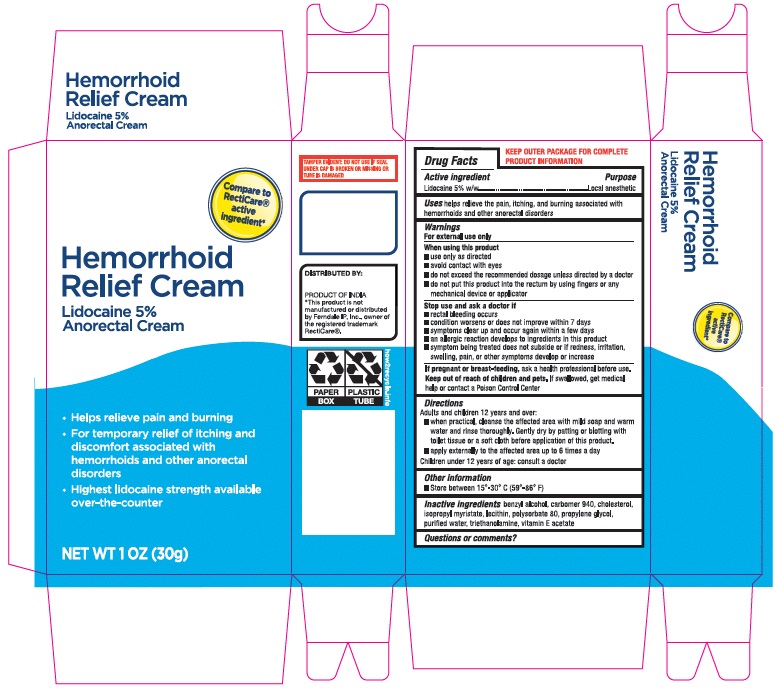 DRUG LABEL: Hemorrhoid Relief Cream
NDC: 73492-712 | Form: CREAM
Manufacturer: ALAINA HEALTHCARE PRIVATE LIMITED
Category: otc | Type: HUMAN OTC DRUG LABEL
Date: 20251209

ACTIVE INGREDIENTS: LIDOCAINE 50 mg/1 g
INACTIVE INGREDIENTS: BENZYL ALCOHOL; CARBOMER 940; CHOLESTEROL; ISOPROPYL MYRISTATE; LECITHIN, SOYBEAN; POLYSORBATE 80; PROPYLENE GLYCOL; WATER; TROLAMINE; .ALPHA.-TOCOPHEROL ACETATE

Hemorrhoid Relief Cream
Lidocaine 5% Anorectal Cream

Drug Facts

Active Ingredient

Lidocaine 5% W/W

Purpose

Local Anesthetic

Uses

helps relieve the pain, itching, and burning associated with hemorrhoids and other anorectal disorders.

Warnings

For external use only

When using this product

- use only as directed.
- Avoid contact with eyes.
- do not exceed the recommended dosage unless directed by a doctor.
- do not put this product into the rectum by using fingers or any mechanical device or applicator.

Stop use and ask a doctor if

- rectal bleeding occurs.
- condition worsens or does not improve within 7 days.
- symptoms clear up and occur again within a few days.
- an allergic reaction develops to ingredients in this product.
- symptom being treated does not subside or if redness, irritation, swelling, pain, or other symptoms develop or increase.

If pregnant or breast-feeding, ask a health professional before use.

Keep out of reach of children and pets.If swallowed, get medical help or contact a Poison Control Center.

Directions

Adult and children 12 years and over:

- When practical, cleanse the affected area with mild soap and warm water and rinse thoroughly.
- gently dry by patting or blotting with toilet tissue or a soft cloth before application of this product.
- apply externally to the affected area up to 6 times a day
- children under 12 years of age: consult a doctor.

Other Information.

- Store between 15°-30° C (59°-86°F).

Inactive Ingredient

Benzyl Alcohol, Carbomer 940, Cholesterol, Isopropyl Myristate, Lecithin, Polysorbate 80, Propylene Glycol, Purified Water, Triethanolamine, Vitamin-E Acetate.

*This product is not manufactured or distributed by Ferndale IP, Inc., Owner of the registered trademark RectiCare®.

PACKAGE LABEL.PRINCIPAL DISPLAY PANEL

Hemorrhoid Relief Cream
Lidocaine 5% Anorectal Cream
Helps relieve pain and burning
For temporary relief of itching and discomfort associated with hemorrhoids and other anorectal disorders
Highest lidocaine strength available over-the-counter
Net wt 1oz (30g)